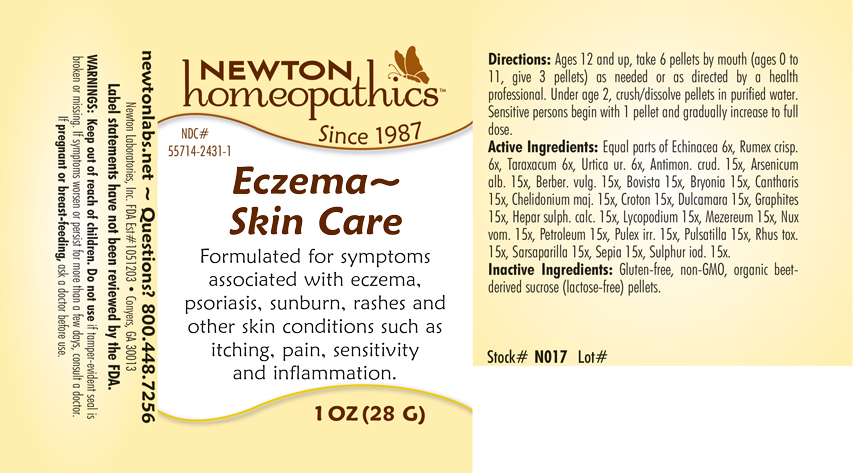 DRUG LABEL: Eczema - Skin Care
NDC: 55714-2431 | Form: PELLET
Manufacturer: Newton Laboratories, Inc.
Category: homeopathic | Type: HUMAN OTC DRUG LABEL
Date: 20201125

ACTIVE INGREDIENTS: SARSAPARILLA 15 [hp_X]/1 g; ANTIMONY TRISULFIDE 15 [hp_X]/1 g; ARSENIC TRIOXIDE 15 [hp_X]/1 g; BERBERIS VULGARIS ROOT BARK 15 [hp_X]/1 g; GIANT PUFFBALL 15 [hp_X]/1 g; BRYONIA ALBA ROOT 15 [hp_X]/1 g; LYTTA VESICATORIA 15 [hp_X]/1 g; CHELIDONIUM MAJUS 15 [hp_X]/1 g; CROTON TIGLIUM SEED 15 [hp_X]/1 g; SOLANUM DULCAMARA TOP 15 [hp_X]/1 g; GRAPHITE 15 [hp_X]/1 g; CALCIUM SULFIDE 15 [hp_X]/1 g; LYCOPODIUM CLAVATUM SPORE 15 [hp_X]/1 g; DAPHNE MEZEREUM BARK 15 [hp_X]/1 g; STRYCHNOS NUX-VOMICA SEED 15 [hp_X]/1 g; KEROSENE 15 [hp_X]/1 g; PULEX IRRITANS 15 [hp_X]/1 g; PULSATILLA VULGARIS 15 [hp_X]/1 g; TOXICODENDRON PUBESCENS LEAF 15 [hp_X]/1 g; SEPIA OFFICINALIS JUICE 15 [hp_X]/1 g; SULFUR IODIDE 15 [hp_X]/1 g; ECHINACEA, UNSPECIFIED 6 [hp_X]/1 g; RUMEX CRISPUS ROOT 6 [hp_X]/1 g; TARAXACUM OFFICINALE 6 [hp_X]/1 g; URTICA URENS 6 [hp_X]/1 g
INACTIVE INGREDIENTS: SUCROSE

Eczema 2431P

INDICATIONS & USAGE SECTION

Formulated for symptoms associated with eczema, psoriasis, sunburn, rashes and other skin conditions such as itching, pain, sensitivity and inflammation.

DOSAGE & ADMINISTRATION SECTION

Directions: Ages 12 and up, take 6 pellets by mouth (ages 0 to 11, give 3 pellets) as needed or as directed by a health professional. Under age 2, crush or dissolve pellets in purfied water. Sensitive persons begin with 1 pellet and gradually increase to full dose.

OTC - ACTIVE INGREDIENT SECTION

Equal parts of Echinacea 6x, Rumex crisp. 6x, Taraxacum 6x, Urtica 6x, Antimon. crud. 15x, Arsenicum alb. 15x, Berber. vulg. 15x, Bovista 15x, Bryonia 15x, Cantharis 15x, Chelidonium majus 15x, Croton 15x, Dulcamara 15x, Graphites 15x, Hepar sulph. calc. 15x, Lycopodium 15x, Mezereum 15x, Nux vom. 15x, Petroleum 15x, Pulex irr. 15x, Pulsatilla 15x, Rhus tox. 15x, Sarsaparilla 15x, Sepia 15x, Sulphur iod. 15x.

OTC - PURPOSE SECTION

Formulated for symptoms associated with eczema, psoriasis, sunburn, rashes and other skin conditions such as itching, pain, sensitivity and inflammation.

INACTIVE INGREDIENT SECTION

Inactive Ingredients: Gluten-free, non-GMO, beet-derived sucrose (lactose-free) pellets.

QUESTIONS SECTION

newtonlabs.net - Questions? 800.448.7256

Newton Laboratories, Inc. FDA Est # 1051203 - Conyers, GA 30013

WARNINGS SECTION

WARNINGS: Keep out of reach of children. Do not use if tamper-evident seal is broken or missing. If symptoms worsen or persist for more than a few days, consult a doctor. If pregnant or breast-feeding, ask a doctor before use.

OTC - PREGNANCY OR BREAST FEEDING SECTION

If pregnant or breast-feeding, ask a doctor before use.

OTC - KEEP OUT OF REACH OF CHILDREN SECTION

Keep out of reach of children.